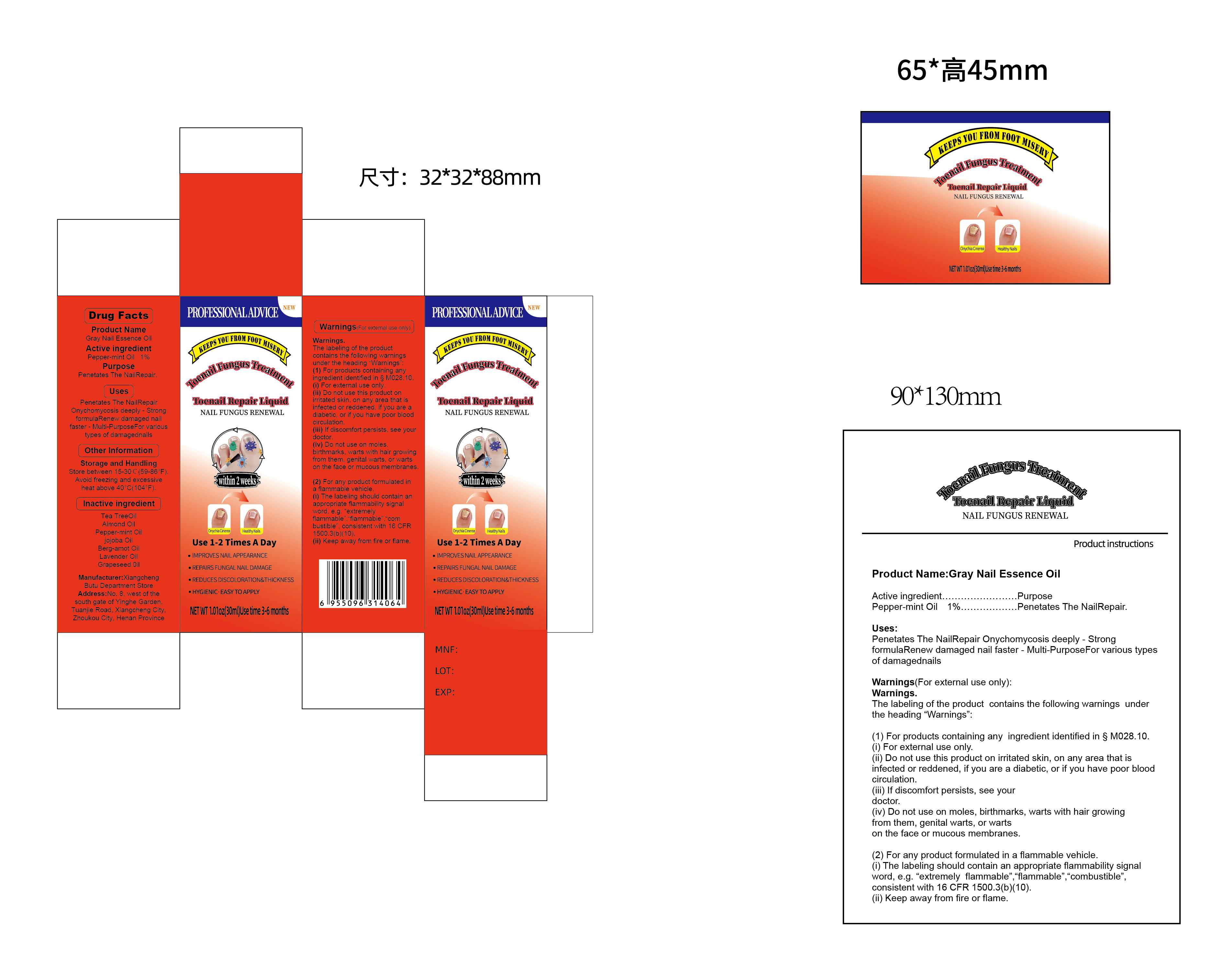 DRUG LABEL: Gray Nail Essence Oil
NDC: 85593-007 | Form: LIQUID
Manufacturer: Guangzhou ChuanMa International Trading Co.,Ltd.
Category: otc | Type: HUMAN OTC DRUG LABEL
Date: 20250813

ACTIVE INGREDIENTS: PEPPERMINT OIL 1 g/100 mL
INACTIVE INGREDIENTS: TEA TREE OIL; ALMOND OIL; BERGAMOT OIL; GRAPEFRUIT OIL; JOJOBA OIL; LAVENDER OIL

Active ingredient.
Pepper-mint Oil 1%... PurposePenetates The NailRepair

Do not use on molesbirthmarks, warts with hair growingfrom them, genital warts, or wartson the face or mucous membranes

WARNINGS

The labeling of the productcontains the following warningsunder the heading "warnings(1)For products containing anyingredient identified in S M028.10(i) For external use only.(ii) Do not use this product onirritated skin, on any area that isinfected or reddened. if you are adiabetic, or if you have poor bloodcirculation

DOSAGE AND ADMINISTRATION

Use 1-2 Times A Day

PURPOSE

Penetates The NailRepair.

INACTIVE INGREDIENT

Tea TreeOilAlmond OilPepper-mint Oiljojoba OilBerg-amot OilLavender OilGrapeseed 0il

INDICATIONS AND USAGE

Penetates The NailRepairOnychomycosis deeply-StrongformulaRenew damaged nailaster-Multi-PurposeFor varioustypes of damagednails

Keep of out reach of children